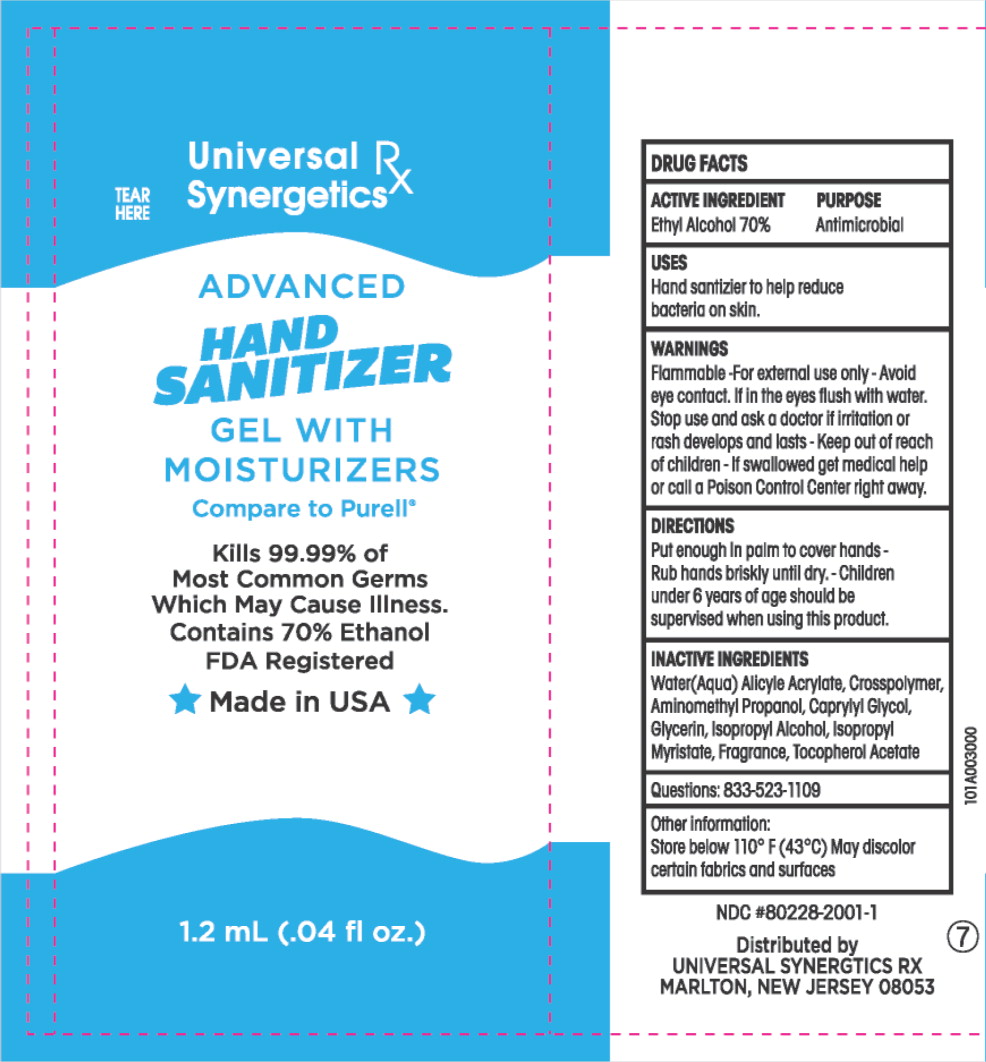 DRUG LABEL: Hand Sanitizer
NDC: 80228-2001 | Form: GEL
Manufacturer: Universal Synergetics, Inc
Category: otc | Type: HUMAN OTC DRUG LABEL
Date: 20250224

ACTIVE INGREDIENTS: ALCOHOL 0.84 mL/1.2 mL
INACTIVE INGREDIENTS: WATER; CARBOMER INTERPOLYMER TYPE A (ALLYL SUCROSE CROSSLINKED); AMINOMETHYLPROPANOL; CAPRYLYL GLYCOL; GLYCERIN; ISOPROPYL ALCOHOL; ISOPROPYL MYRISTATE; .ALPHA.-TOCOPHEROL ACETATE

Universal Synergetics Hand Sanitizer Gel, 1.2mL (.04 fl oz)

ACTIVE INGREDIENT

Ethyl Alcohol 70%

PURPOSE

Antimicrobial

USES

Hand sanitizer to help reduce bacteria on skin.

WARNINGS

Flammable -For external use only - Avoid eye contact. If in the eyes flush with water.

Stop use and ask a doctor if irritation or rash develops and lasts

- Keep out of reach of children - If swallowed get medical help or call a Poison Control Center right away.

DIRECTIONS

Put enough in palm to cover hands - Rub hands briskly until dry. - Children under 6 years of age should be supervised when using this product.

INACTIVE INGREDIENTS

Water(Aqua) Alicyle Acrylate, Crosspolymer, Aminomethyl Propanol, Caprylyl Glycol, Glycerin, Isopropyl Alcohol, Isopropyl Myristate, Fragrance, Tocopherol Acetate

Questions: 833-523-1109

Other information:

Store below 110° F (43°C) May discolor certain fabrics and surfaces